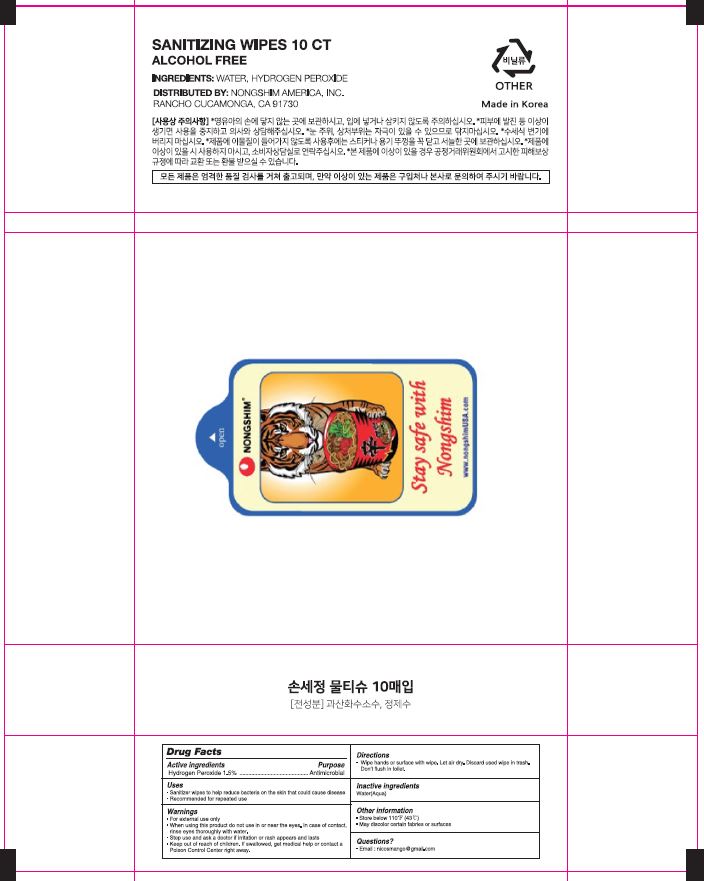 DRUG LABEL: TRIZ sanitizer wipes
NDC: 74719-0005 | Form: CLOTH
Manufacturer: G-CLEAN
Category: otc | Type: HUMAN OTC DRUG LABEL
Date: 20200603

ACTIVE INGREDIENTS: HYDROGEN PEROXIDE 0.6684 g/44.56 g
INACTIVE INGREDIENTS: WATER

G-CLEAN - TRIZ sanitizer wipes

ACTIVE INGREDIENT

Hydrogen Peroxide 1.5%

INACTIVE INGREDIENT

WATER

PURPOSE

Sanitizer wipes to help reduce bacteria on the skin that could cause disease

Recommended for repeated use

keep out of reach of the children

INDICATIONS AND USAGE

Wipe hands or surface with wipe. Let air dry. Discard used wipe in trash. Don't flush in toilet.

WARNINGS

For external use only
When using this product do not use in or near the eyes. In case of contact, rinse eyes thoroughly with water
Stop use and ask a doctor if irritation or rash appears and lasts
Keep out of reach of children. If swallowed, get medical help or contact a Poison Control Center right away

DOSAGE AND ADMINISTRATION

for external use only